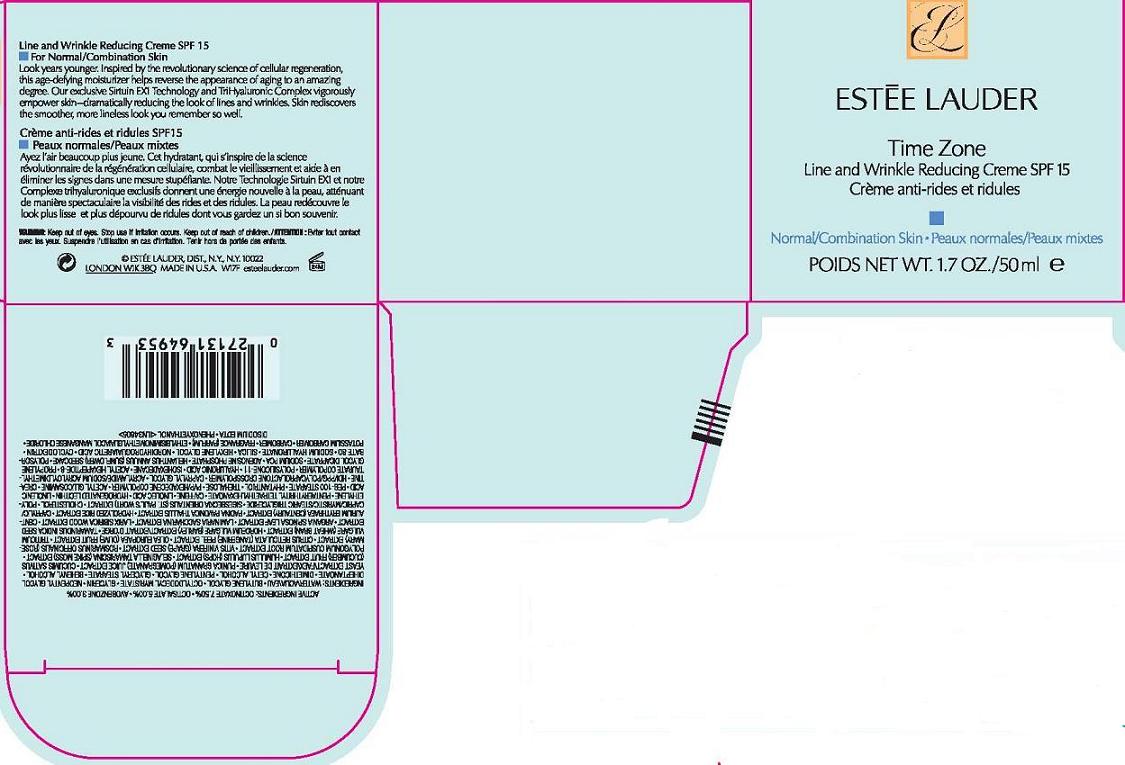 DRUG LABEL: TIME ZONE
NDC: 11559-737 | Form: CREAM
Manufacturer: ESTEE LAUDER INC
Category: otc | Type: HUMAN OTC DRUG LABEL
Date: 20110722

ACTIVE INGREDIENTS: OCTINOXATE 7.5 mL/100 mL; OCTISALATE 5.0 mL/100 mL; AVOBENZONE 3.0 mL/100 mL
INACTIVE INGREDIENTS: WATER; BUTYLENE GLYCOL; GLYCERIN; DIMETHICONE; CETYL ALCOHOL; GLYCERYL MONOSTEARATE; SACCHAROMYCES LYSATE; CUCUMBER; OLIVE OIL; BARLEY; TAMARIND SEED; SACCHARINA LATISSIMA WHOLE; CHOLESTEROL; HIGH DENSITY POLYETHYLENE; LINOLEIC ACID; TREHALOSE; CREATINE; CAPRYLYL GLYCOL; POLYSORBATE 60; HYALURONATE SODIUM; SILICON DIOXIDE; CARBOMER HOMOPOLYMER TYPE C; EDETATE DISODIUM; PHENOXYETHANOL

ACTIVE INGREDIENT

ACTIVE INGREDIENTS: OCTINOXATE 7.50% [] OCTISALATE 5.00% [] AVOBENZONE 3.00%

INACTIVE INGREDIENT

INACTIVE INGREDIENTS: WATER [] BUTYLENE GLYCOL [] OCTYLDODECYL MYRISTATE [] GLYCERIN [] NEOPENTYL GLYCOL DIHEPTANOATE [] DIMETHICONE [] CETYL ALCOHOL [] PENTYLENE GLYCOL [] GLYCERYL STEARATE [] BEHENYL ALCOHOL [] YEAST EXTRACT\FAEX\EXTRAIT DE LEVURE [] PUNICA GRANATUM (POMEGRANATE) JUICE EXTRACT [] CUCUMIS SATIVUS (CUCUMBER) FRUIT EXTRACT [] HUMULUS LUPULUS (HOPS) EXTRACT [] SELAGINELLA TAMARISCINA (SPIKE MOSS) EXTRACT [] POLYGONUM CUSPIDATUM ROOT EXTRACT [] VITIS VINIFERA (GRAPE) SEED EXTRACT [] ROSMARINUS OFFICINALIS (ROSEMARY) EXTRACT [] CITRUS RETICULATA (TANGERINE) PEEL EXTRACT [] OLEA EUROPAEA (OLIVE) FRUIT EXTRACT [] TRITICUM VULGARE (WHEAT BRAN) EXTRACT [] HORDEUM VULGARE (BARLEY) EXTRACT\EXTRAIT D'ORGE [] TAMARINDUS INDICA SEED EXTRACT [] ARGANIA SPINOSA LEAF EXTRACT [] LAMINARIA SACCHARINA EXTRACT [] LARIX SIBIRICA WOOD EXTRACT [] CENTAURIUM ERYTHRAEA (CENTAURY) EXTRACT [] PADINA PAVONICA THALLUS EXTRACT [] HYDROLYZED RICE EXTRACT [] CAPRYLIC/CAPRIC/MYRISTIC/STEARIC TRIGLYCERIDE [] SIGESBECKIA ORIENTALIS EXTRACT [] CHOLESTEROL [] POLYETHYLENE [] PENTAERYTHRITYL TETRAETHYLHEXANOATE [] CAFFEINE [] LINOLEIC ACID [] HYDROGENATED LECITHIN [] LINOLENIC ACID [] PEG-100 STEARATE [] PHYTANTRIOL [] TREHALOSE [] PVP/HEXADECENE COPOLYMER [] ACETYL GLUCOSAMINE [] CREATINE [] HDI/PPG/POLYCAPROLACTONE CROSSPOLYMER [] CAPRYLYL GLYCOL [] ACRYLAMIDE/SODIUM ACRYLOYLDIMETHYLTAURATE COPOLYMER [] POLYSILICONE-11 [] HYALURONIC ACID [] ISOHEXADECANE [] ACETYL HEXAPEPTIDE-8 [] PROPYLENE GLYCOL DICAPRATE [] SODIUM PCA [] ADENOSINE PHOSPHATE [] HELIANTHUS ANNUUS (SUNFLOWER) SEEDCAKE [] POLYSORBATE 80 [] SODIUM HYALURONATE [] SILICA [] HEXYLENE GLYCOL [] NORDIHYDROGUAIARETIC ACID [] CYCLODEXTRIN [] POTASSIUM CARBOMER [] CARBOMER [] FRAGRANCE (PARFUM) [] ETHYLBISIMINOMETHYLGUAIACOL MANGANESE CHLORIDE [] DISODIUM EDTA [] PHENOXYETHANOL

WARNINGS

WARNING: KEEP OUT OF EYES. STOP USE IF IRRITATION OCCURS.

KEEP OUT OF REACH OF CHILDREN

PACKAGE LABEL

PRINCIPAL DISPLAY PANEL:
ESTEE LAUDER
TIME ZONE
LINE AND WRINKLE REDUCING CREAM
SPF 15
NORMAL/COMBINATION SKIN
1.7 OZ/ 50 ML
ESTEE LAUDER DISTR.
NY, NY 10022